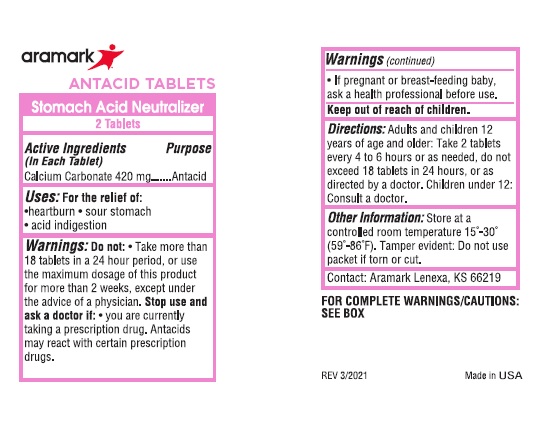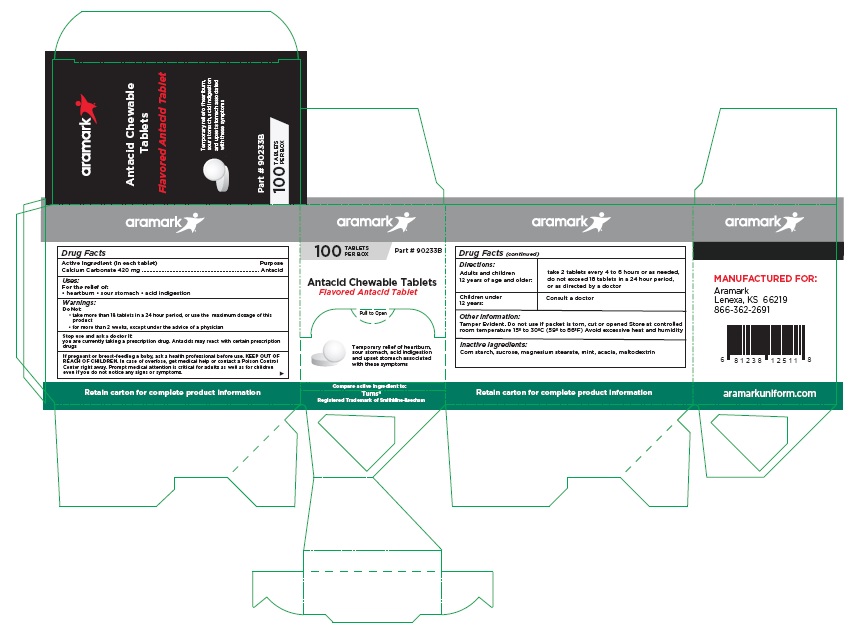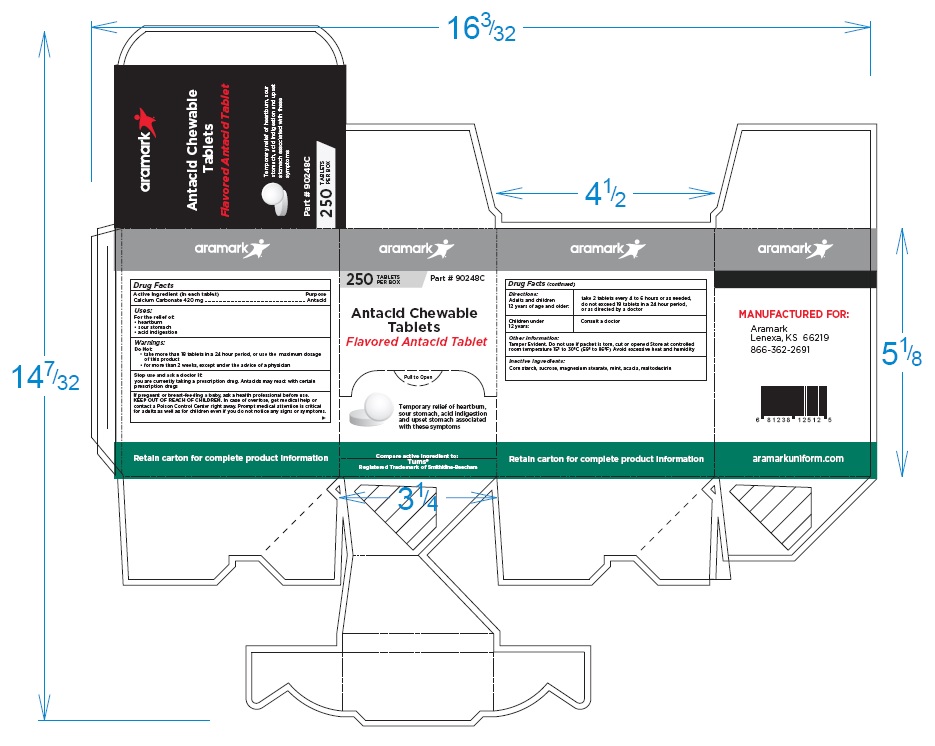 DRUG LABEL: Aramark Antacid Chewable
NDC: 81238-0303 | Form: TABLET
Manufacturer: Western First Aid Safety DBA Aramark
Category: otc | Type: HUMAN OTC DRUG LABEL
Date: 20210601

ACTIVE INGREDIENTS: CALCIUM CARBONATE 420 mg/1 1
INACTIVE INGREDIENTS: STARCH, CORN; SUCROSE; MAGNESIUM STEARATE; MINT; ACACIA; MALTODEXTRIN

Aramark Antacid Chewable Tablets

Drug Facts

Active Ingredient (in each tablet)
Calcium Carbonate 420 mg

Purpose
Calcium Carbonate ............. Antacid

Uses:
For the relief of:
• heartburn • sour stomach • acid indigestion

WARNINGS

Warnings: Do Not:• take more than 18 tablets in a 24 hour period, or use the maximum dosage of this
product
• for more than 2 weeks, except under the advice of a physician

Stop use and ask a doctor if:
you are currently taking a prescription drug. Antacids may react with certain prescription
drugs

PREGNANCY OR BREAST FEEDING

If pregnant or breast-feeding a baby, ask a health professional before use.

Keep out of reach of children In case of overfose, get medical help or contact a Poison Control
Center right away. Prompt medical attention is critical for adults as well as for children
even if you do not notice any signs or symptoms.

DOSAGE AND ADMINISTRATION

Directions: Adults and children 12 years of age and older: | do not exceed 18 tablets in a 24 hour period, or as directed by a doctor
Children under 12 years: | Consult a doctor

Other information:
Tamper Evident. Do not use if packet is torn, cut or opened Store at controlled
room temperature 15º to 30ºC (59º to 86ºF) Avoid excessive heat and humidity

Inactive Ingredients:
Corn starch, sucrose, magnesium stearate, mint, acacia, maltodextrin

Package Labeling

aramark

100TABLETS Part # 90233B
PER BOX

Antacid Chewable Tablets
Flavored Antacid Tablet

Temporary relief of heartburn,
sour stomach, acid indigestion
and upset stomach associated
with these symptoms

Compare active ingredient to:

Tums® aramarkuniform.com
Registered Trademark of Smithkline-Beecham

MANUFACTURED FOR:

Aramark
Lenexa, KS 66219
866-362-2691

aramarkuniform.com

Retain carton for complete product information

100 Tablet Box

250 Tablet Box

2-Tablet Packet

res